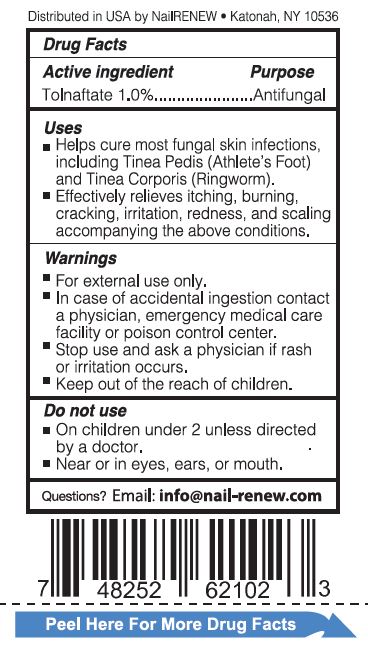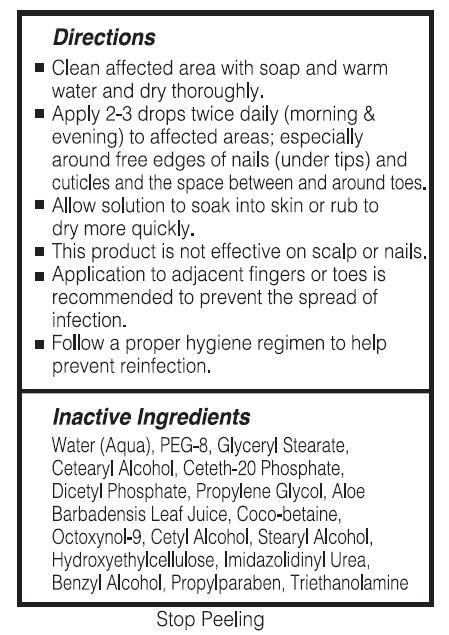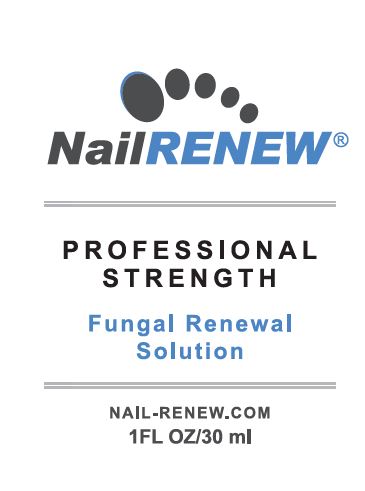 DRUG LABEL: NAIL RENEW
NDC: 62858-101 | Form: LIQUID
Manufacturer: Nailrenew Corp
Category: otc | Type: HUMAN OTC DRUG LABEL
Date: 20240110

ACTIVE INGREDIENTS: TOLNAFTATE 1 g/100 mL
INACTIVE INGREDIENTS: WATER; POLYETHYLENE GLYCOL 400; GLYCERYL MONOSTEARATE; CETOSTEARYL ALCOHOL; CETETH-20 PHOSPHATE; DIHEXADECYL PHOSPHATE; PROPYLENE GLYCOL; ALOE VERA LEAF; COCO-BETAINE; OCTOXYNOL-9; CETYL ALCOHOL; STEARYL ALCOHOL; HYDROXYETHYL CELLULOSE (100 MPA.S AT 2%); IMIDUREA; BENZYL ALCOHOL; PROPYLPARABEN; TROLAMINE

NAILRENEW (62858-101)

ACTIVE INGREDIENT

TOLNAFTATE 1.0%

PURPOSE

ANTIFUNGAL

USES

- Helps cure most fungal nail and skin infections, including Tinea Corporis (Ringworm) and Tinea Pedis (Athlete's Foot).
- Effectively relieves itching, burning, cracking and scaling accompanying the above conditions.

WARNINGS

- For external use only.
- In case of accidental ingestion contact a physician, emergency medical care facility or poison control center.
- Stop use and ask a physician if rash or irritation occurs.

KEEP OUT OF REACH OF CHILDREN.

DO NOT USE

- ON CHILDREN UNDER 2 UNLESS DIRECTED BY A DOCTOR.
- NEAR OR IN EYES, EARS OR MOUTH.

QUESTIONS? EMAIL: INFO@NAIL-RENEW.COM

DIRECTIONS

- Clean affected area with soap and warm water and dry thoroughly.
- Apply 2-3 drops twice daily (morning & evening) to affected areas; especially around free edges of nails (under tips) and cuticles and the space around the toes.
- Allow solution to soak into nail or skin.
- This product is not effective on scalp or hair.
- Application to adjacent nails is recommended to prevent the spread of the infection. Keep affected areas clean and dry throughout the day.

INACTIVE INGREDIENT

Water (Aqua), PEG-8, Glyceryl Stearate, Cetearyl Alcohol, Ceteth-20 Phosphate, Dicetyl Phosphate, Propylene Glycol, Aloe Barbadensis Leaf Juce, Coco-betaine, Octoxynol-9, Cetyl Alcohol, Stearyl Alcohol, Hydroxyethylcellulose, Imidazolidinyl Urea, Benzyl Alcohol, Propylparaben, Triethanolamine